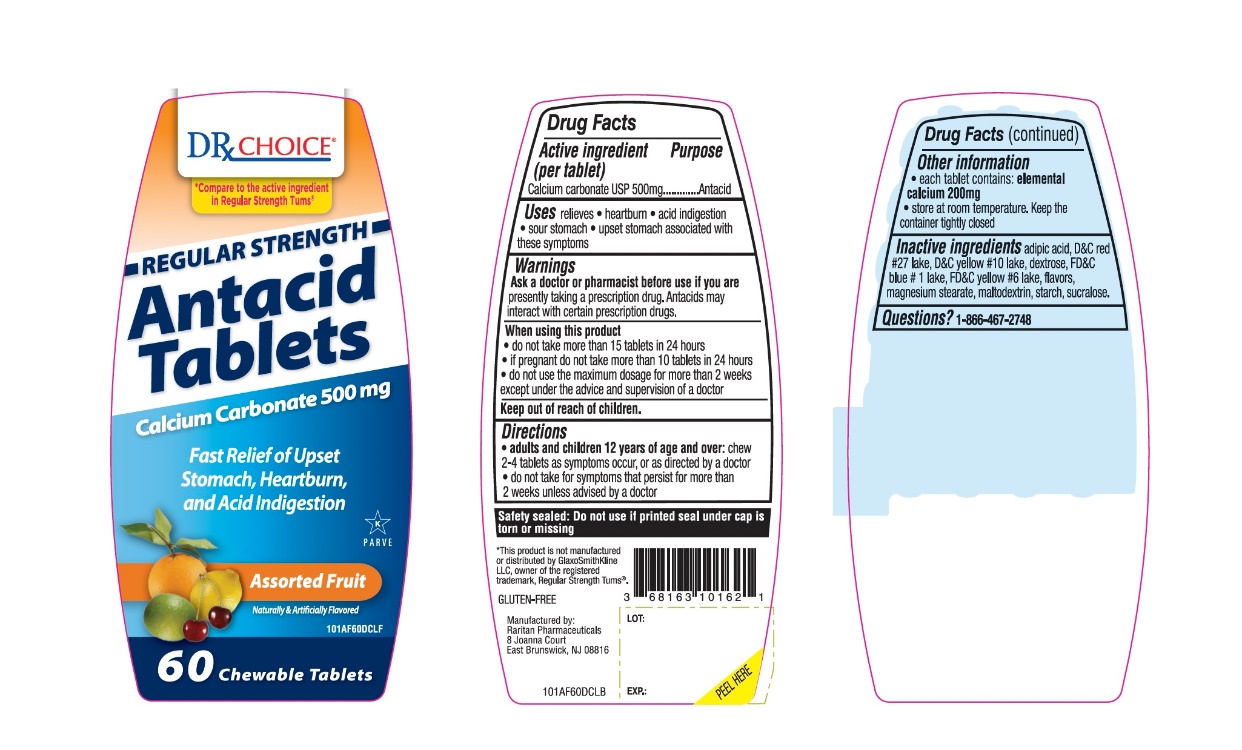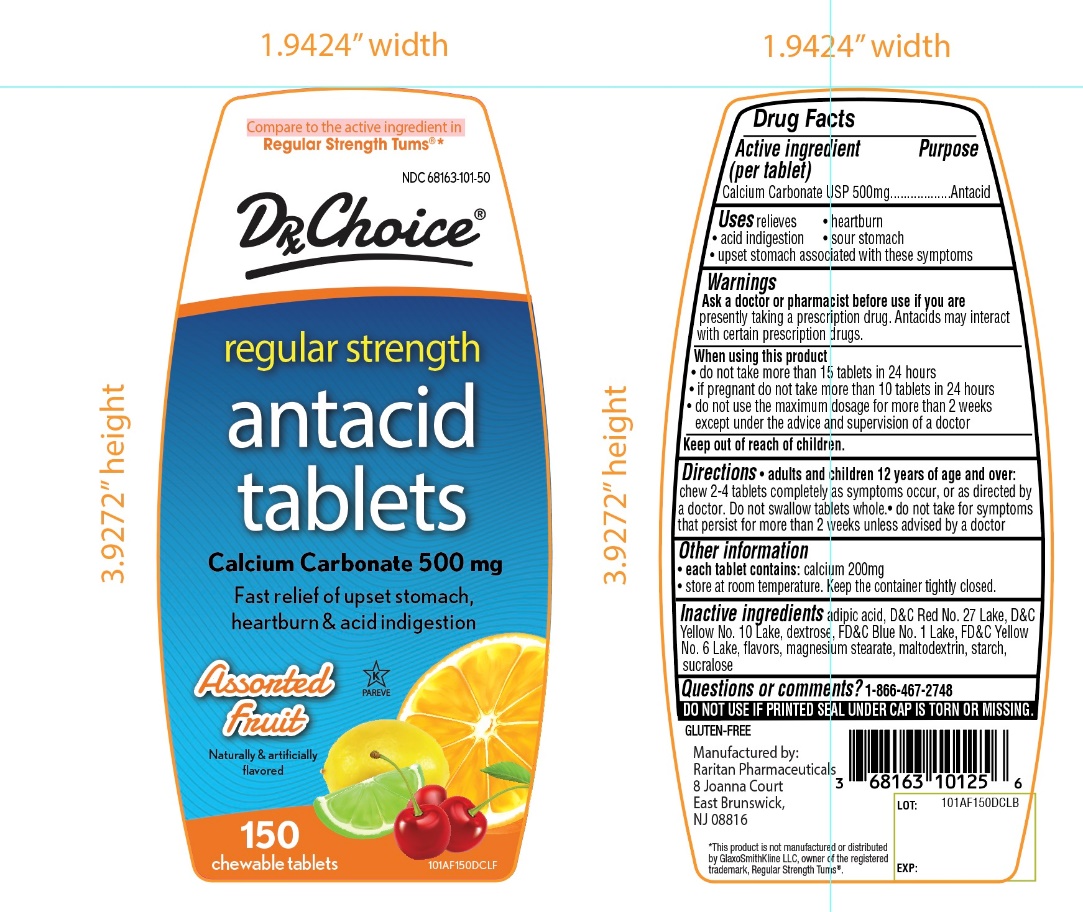 DRUG LABEL: DRx CHOICE Antacid Calcium

NDC: 68163-101 | Form: TABLET, CHEWABLE
Manufacturer: Raritan Pharmaceuticals Inc
Category: otc | Type: HUMAN OTC DRUG LABEL
Date: 20250926

ACTIVE INGREDIENTS: CALCIUM CARBONATE 500 mg/1 1
INACTIVE INGREDIENTS: ADIPIC ACID; D&C RED NO. 27; D&C YELLOW NO. 10; DEXTROSE, UNSPECIFIED FORM; FD&C BLUE NO. 1; FD&C YELLOW NO. 6; MAGNESIUM STEARATE; MALTODEXTRIN; STARCH, CORN; SUCRALOSE

DRx Choice Regular Strength Antacid Calcium Assorted Fruit Chewable Tablets Drug Facts

Active ingredient (per tablet)

Calcium Carbonate USP 500mg

Purpose

Antacid

Uses

relieves

- heartburn
- acid indigestion
- sour stomach
- upset stomach associated with these symptoms

Warnings

Ask a doctor or pharmacist before use if you are

presently taking a prescription drug. Antacids may interact with certain prescription drugs.

When using this product

- do not take more than 15 tablets in 24 hours
- if pregnant do not take more than 10 tablets in 24 hours
- do not use the maximum dosage for more than 2 weeks except under the advice and supervision of a doctor

Directions

- adults and children 12 years of age and over:chew 2-4 tablets as symptoms occur, or as directed by a doctor. Do not swallow tablets whole.
- do not take for symptoms that persist for more than 2 weeks unless advised by a doctor

Other information

- each tablet contains:elemental calcium 200mg
- store at room temperature. Keep the container tightly closed.

Inactive ingredients

adipic acid, D&C Red No. 27, D&C Yellow No. 10 dextrose, FD&C Blue No. 1, FD&C Yellow No. 6, flavors, magnesium stearate, maltodextrin, starch, sucralose.

Questions?

1-866-467-2748

Principal Display Panel

DRx CHOICE®

*Compare to the active Ingredient in Regular Strength Tums®

REGULAR STRENGTH

Antacid Tablets

CALCIUM CARBONATE 500 mg

Fast Relief of Upset Stomach, Heartburn and Acid Indigestion.

Assorted Fruit

Naturally & Artificially Flavored

GLUTEN-FREE

Chewable Tablets 60

K PAREVE

DO NOT USE IF PRINTED SEAL UNDER CAP IS BROKEN OR MISSING.

*This product is not manufactured or distributed by GlaxoSmithKline LLC, owner of the registered trademark, Regular Strength Tums®.

Manufactured by: Raritan Pharmaceuticals

8 Joanna Court, East Brunswick, NJ 08816

Package label for 60ct Tablets

Principal Display Panel

Package label for 150ct Tablets